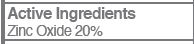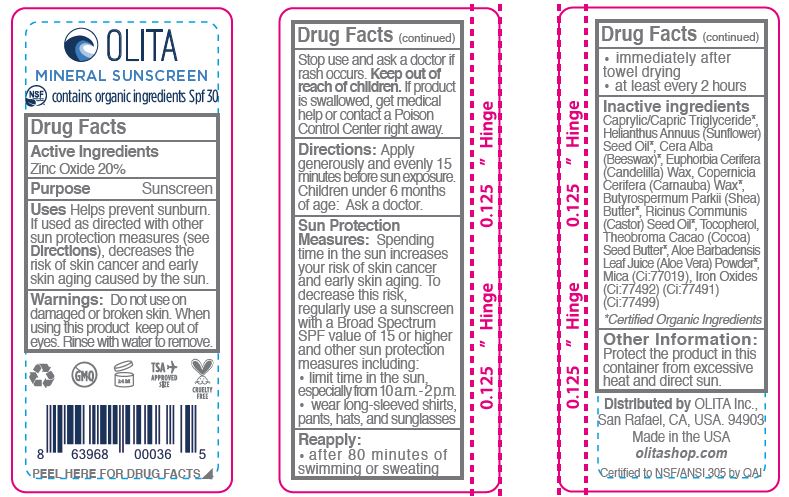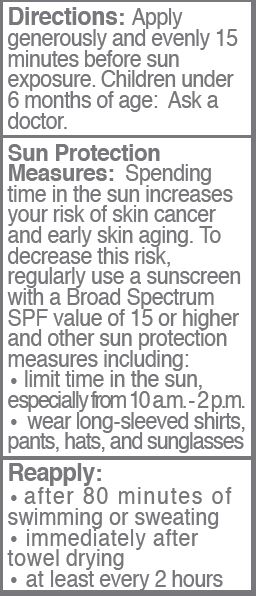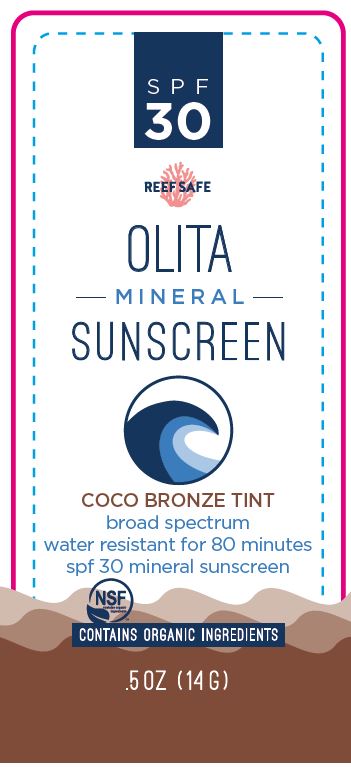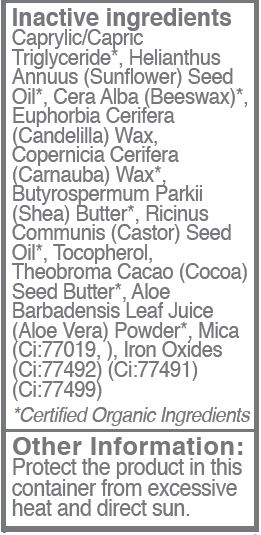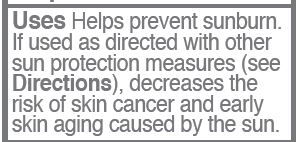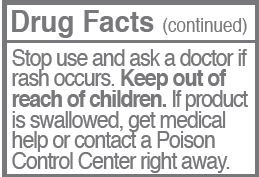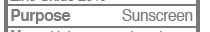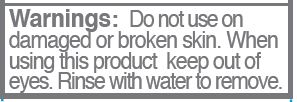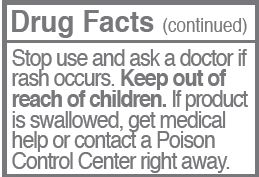 DRUG LABEL: Sunscreen
NDC: 62932-215 | Form: STICK
Manufacturer: Private Label Select Ltd CO
Category: otc | Type: HUMAN OTC DRUG LABEL
Date: 20200320

ACTIVE INGREDIENTS: ZINC OXIDE 20 g/100 g
INACTIVE INGREDIENTS: COCONUT OIL; SUNFLOWER OIL; ALOE VERA LEAF; MICA; FERRIC OXYHYDROXIDE; CARNAUBA WAX; COCOA BUTTER; SHEA BUTTER; .BETA.-TOCOPHEROL; CASTOR OIL; FERRIC OXIDE RED; FERROSOFERRIC OXIDE; WHITE WAX; CANDELILLA WAX

Olita Mineral Sunscreen Coco Bronze Tint, SPF 30